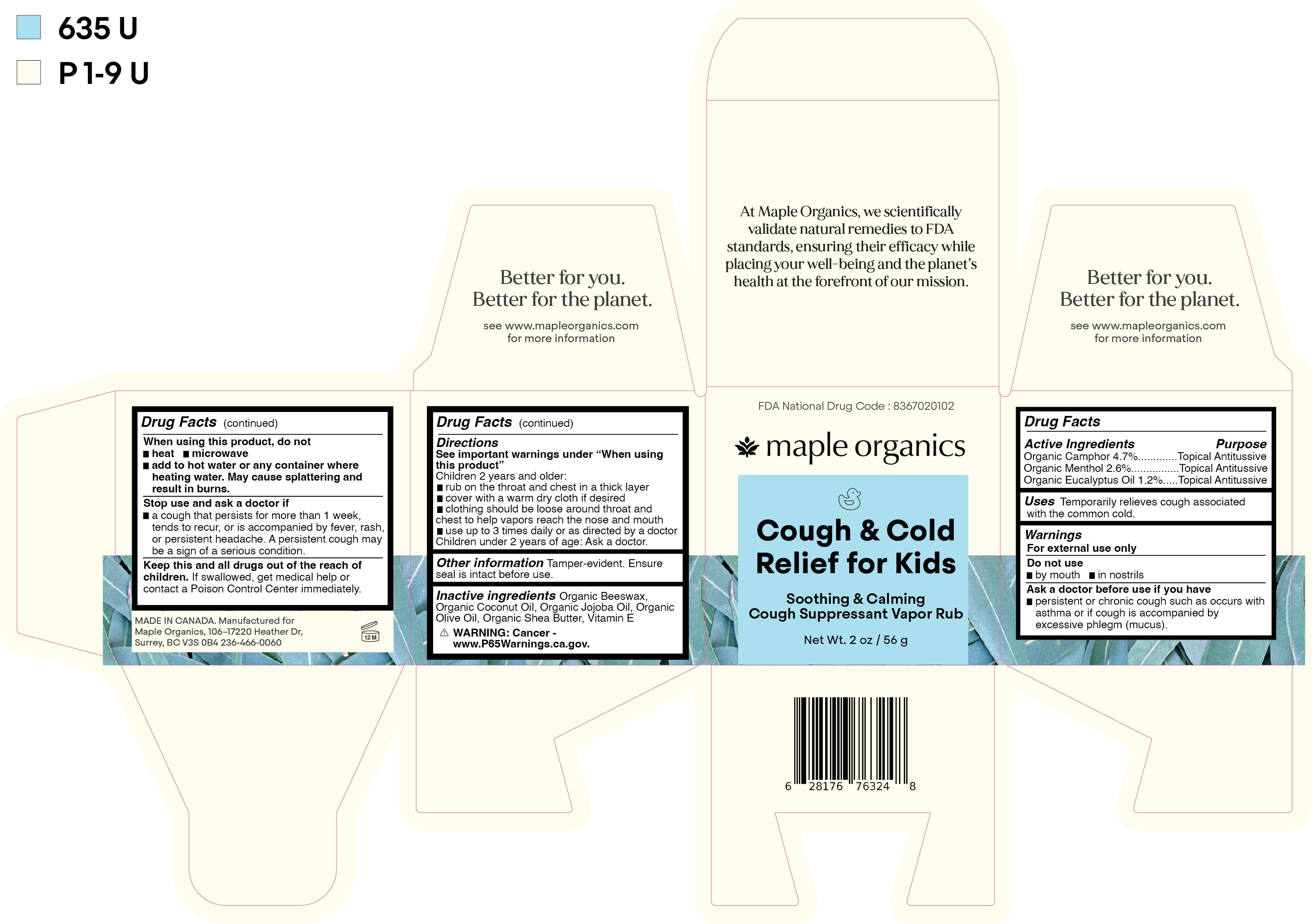 DRUG LABEL: Cough and Cold Therapy For Kids
NDC: 83670-201 | Form: OINTMENT
Manufacturer: Everlaan Organics Inc
Category: otc | Type: HUMAN OTC DRUG LABEL
Date: 20250127

ACTIVE INGREDIENTS: CAMPHOR (NATURAL) 4.7 g/100 g; MENTHOL 2.6 g/100 g; EUCALYPTUS OIL 1.2 g/100 g
INACTIVE INGREDIENTS: YELLOW WAX; JOJOBA OIL; SHEA BUTTER; COCONUT OIL; .ALPHA.-TOCOPHEROL; OLIVE OIL

Cough & Cold Therapy For Kids

Active ingredients

Organic Camphor 4.7%

Organic Menthol 2.6%

Organic Eucalyptus Oil 1.2%

Purpose

Organic Camphor 4.7%......................Topical Antitussive

Organic Menthol 2.6%........................Topical Antitussive

Organic Eucalyptus Oil 1.2%..............Topical Antitussive

Uses

Temporarily relieves cough associated with the common cold.

Warnings

For external use only

Do not use

- by mouth
- in nostrils

Ask a doctor before use if you have

- persistent or chronic cough such as occurs with asthma or if cough is accompanied by excessive phlegm (mucus).

When using this product, do not

- heat
- microwave
- add to hot water or any container where heating water. May cause splattering and result in burns.

Stop use and ask a doctor if

- a cough that persists for more than 1 week, tends to recur, or is accompanied by fevrer, rash, or persistent headache. A persistent cough may be a sign of a serious condition.

KEEP OUT OF REACH OF CHILDREN

Keep this and all drugs out of the reach of children. If swallowed, get medical help or contact a Poison Control Center immediately.

Directions

See important warnings under "When using this product"

Children 2 years and older:

- rub on the throat and chest in a thick layer
- cover with a warm dry cloth if desired
- clothing should be loose about throat and chest to help vapors reach the nose and mouth
- use up to 3 times daily or as directed by a doctor

Children under 2 years of age: Ask a doctor.

Other information

Tamper-evdent. Ensure seal is intact before use.

Inactive ingredients

Organic Beeswax, Organic Coconut Oil, Organic Jojoba Oil, Organic Olive Oil, Organic Shea Butter, Vitamin E.

PACKAGE LABEL

maple organics

Cough & Cold Therapy For Kids

Soothing & Calming Cough Suppressant

Net Wt. 2 oz / 56 g